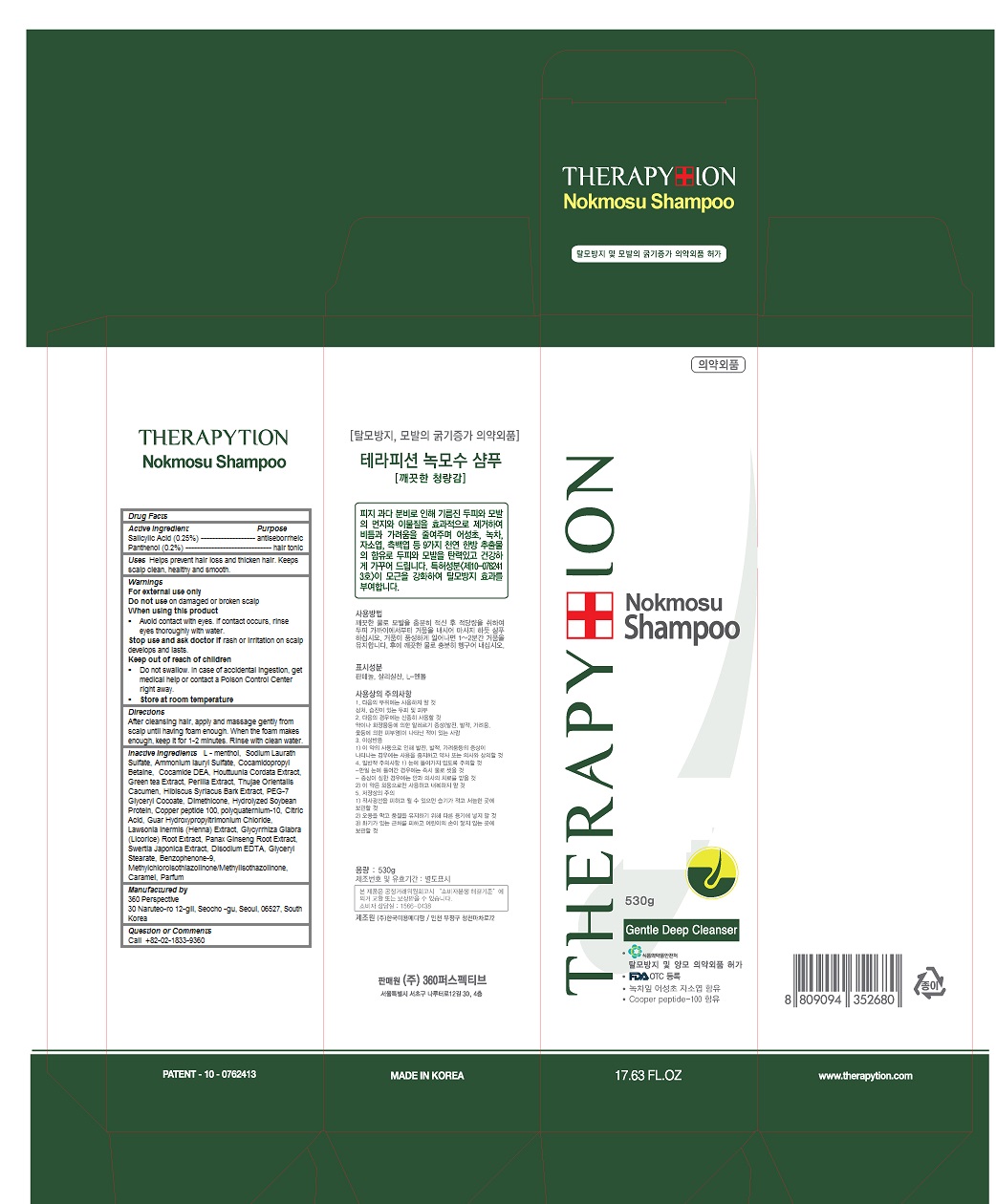 DRUG LABEL: Theraphytion Nokmosu
NDC: 70477-102 | Form: SHAMPOO
Manufacturer: 360 Perspective
Category: otc | Type: HUMAN OTC DRUG LABEL
Date: 20160302

ACTIVE INGREDIENTS: Panthenol 0.002 1/530 g; Salicylic Acid 0.0025 1/530 g
INACTIVE INGREDIENTS: LEVOMENTHOL; SODIUM LAURETH-3 SULFATE; AMMONIUM LAURYL SULFATE; Cocamidopropyl Betaine; COCO DIETHANOLAMIDE; HOUTTUYNIA CORDATA FLOWERING TOP; GREEN TEA LEAF; HIBISCUS SYRIACUS BARK; PEG-7 GLYCERYL COCOATE; Dimethicone; CITRIC ACID MONOHYDRATE; GUAR HYDROXYPROPYLTRIMONIUM CHLORIDE (1.7 SUBSTITUENTS PER SACCHARIDE); GLYCYRRHIZA GLABRA; ASIAN GINSENG; SWERTIA JAPONICA WHOLE FLOWERING; EDETATE DISODIUM; GLYCERYL MONOSTEARATE; Benzophenone-9; Caramel

Theraphytion Nokmosu Shampoo